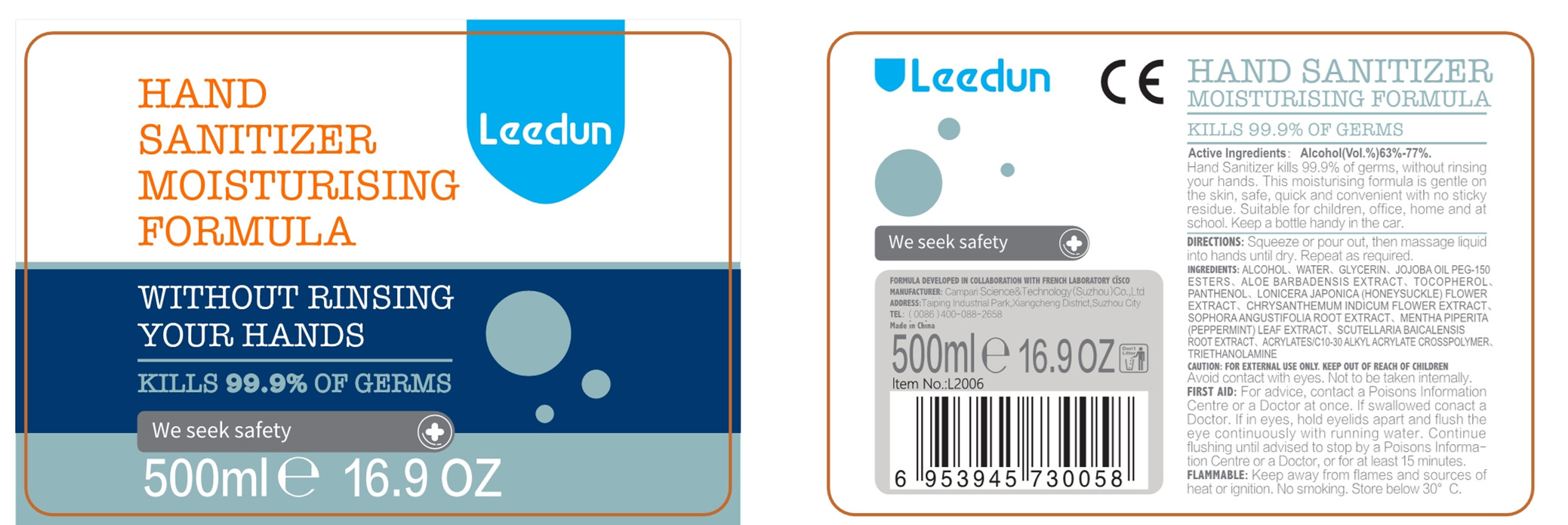 DRUG LABEL: Hand Sanitizer
NDC: 54837-003 | Form: GEL
Manufacturer: Campari Science & Technology (Suzhou) Co., Ltd.
Category: otc | Type: HUMAN OTC DRUG LABEL
Date: 20200528

ACTIVE INGREDIENTS: ALCOHOL 350 mL/500 mL
INACTIVE INGREDIENTS: SCUTELLARIA BAICALENSIS ROOT; TROLAMINE; CARBOMER INTERPOLYMER TYPE A (ALLYL SUCROSE CROSSLINKED); PANTHENOL; WATER; LONICERA JAPONICA FLOWER; GLYCERIN; ALOE VERA LEAF; TOCOPHEROL; CHRYSANTHEMUM INDICUM FLOWER; SOPHORA FLAVESCENS ROOT; MENTHA PIPERITA LEAF

Purpose

Antiseptic, Hand Sanitizer

Use

Hand Sanitizer to help reduce bacteria that potentially can cause disease. For use when soap and water are not available.

Warnings

For external use only. Flammable. Keep away from heat or flame

Do not use

- in children less than 2 months of age
- on open skin wounds

When using this product keep out of eyes, ears, and mouth. In case of contact with eyes, rinse eyes thoroughly with water.
Stop use and ask a doctor if irritation or rash occurs. These may be signs of a serious condition.
Keep out of reach of children. If swallowed, get medical help or contact a Poison Control Center right away.

Stop use and ask a doctor if irritation or rash occurs. These may be signs of a serious condition.

Keep out of reach of children. If swallowed, get medical help or contact a Poison Control Center right away.

Directions

- Place enough product on hands to cover all surfaces. Rub hands together until dry.
- Supervise children under 6 years of age when using this product to avoid swallowing.

Other information

- Store between 15-30°C (59-86°F)
- Avoid freezing and excessive heat above 40°C (104°F)

Inactive ingredients

WATER、GLYCERIN、JOJOBA OIL PEG-150 ESTERS、ALOE BARBADENSIS EXTRACT、TOCOPHEROL、PANTHENOL、LONICERA JAPONICA (HONEYSUCKLE) FLOWER EXTRACT、CHRYSANTHEMUM INDICUM FLOWER EXTRACT、SOPHORA ANGUSTIFOLIA ROOT EXTRACT、MENTHA PIPERITA (PEPPERMINT) LEAF EXTRACT、SCUTELLARIA BAICALENSIS ROOT EXTRACT、ACRYLATES/C10-30 ALKYL ACRYLATE CROSSPOLYMER、TRIETHANOLAMINE

Active Ingredient(s)

Alcohol （Vol.%）63%-77%